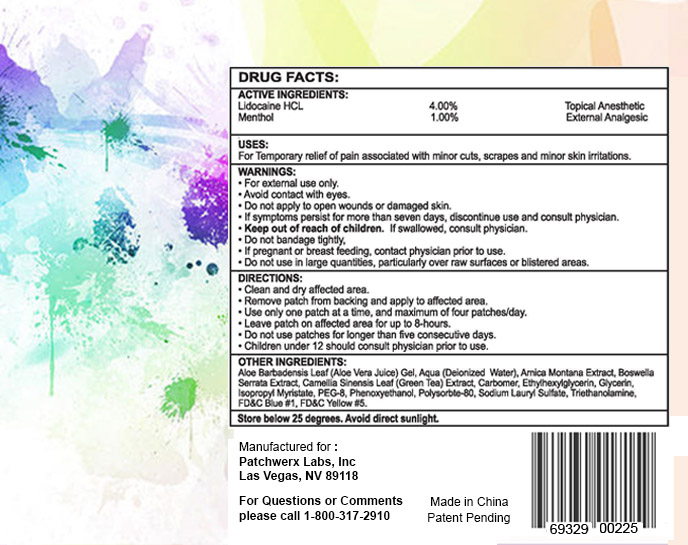 DRUG LABEL: Lidonexe
NDC: 69329-002 | Form: PATCH
Manufacturer: Patchwerx Labs, Inc.
Category: otc | Type: HUMAN OTC DRUG LABEL
Date: 20141118

ACTIVE INGREDIENTS: LIDOCAINE HYDROCHLORIDE 4 g/100 g; MENTHOL 1 g/100 g
INACTIVE INGREDIENTS: INDIAN FRANKINCENSE; GREEN TEA LEAF; ETHYLHEXYLGLYCERIN; GLYCERIN; ISOPROPYL MYRISTATE; POLYETHYLENE GLYCOL 400; PHENOXYETHANOL; POLYSORBATE 80; SODIUM LAURYL SULFATE; TROLAMINE; FD&C BLUE NO. 1; FD&C YELLOW NO. 5; ARNICA MONTANA; ALOE VERA LEAF; water

Lidonexe Patch

Active Ingredients:

Lidocaine HCL 4.00%

Menthol 1.00%

Purpose

Topical Analgesic

External Analgesic

Uses:

For temporary relief of pain associated with minor cuts, scrapes and minor skin irritations.

Warnings

- For external use only
- Avoid contact with eyes
- Do not apply to open wounds or damaged skin.
- If symptoms persist for more than seven days, discontinue use and consult physician.

Keep out of reach of children.

If swallowed, consult physician.

- Do not bandage tightly
- If pregnant or breast feeding, contact physician prior to use.
- Do not use in large quantities, particularly over raw surfaces or blistered areas.

Directions

- Clean and dry affected area.
- Remove patch from backing and apply to affected area.
- Use only one patch at a time, and maximum of four patches/day.
- Leave patch on affected area for up to 8-hours.
- Do not use patches for longer than five consecutive days.
- Children under 12 should consult physician prior to use.

Other Ingredients:

Aloe Barbadensis Leaf (Aloe Vera Juice) Gel, Aqua (Deionized Water), Arnica Montana Extract, Boswellia Serrata Extract, Camellia Sinensis Leaf (Green Tea) Extract, Carbomer, Ethylhexylglycerin, Glycerin, Isopropyl Myristate, PEG-8, Phenoxyethanol, Polysorbate-80, Sodium Lauryl Sulfate, Triethanolamine, FD C Blue 1, FD C Yellow 5.